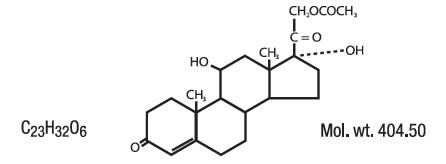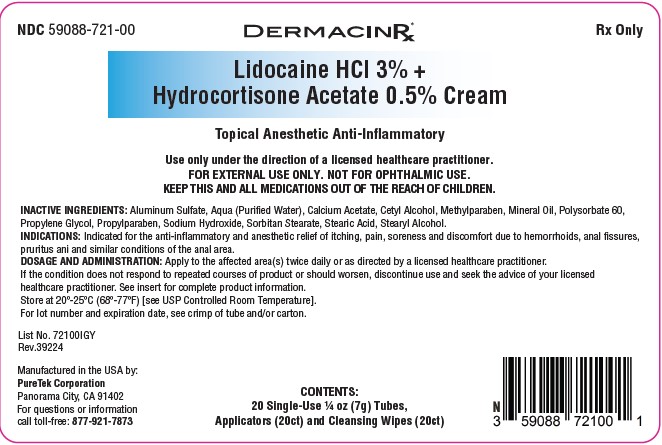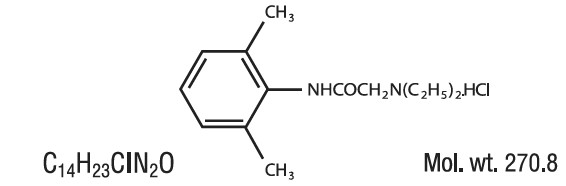 DRUG LABEL: Lidocaine HCl  3% and Hydrocortisone Acetate 0.5% Cream
NDC: 59088-721 | Form: KIT | Route: RECTAL
Manufacturer: PureTek Corporation
Category: prescription | Type: HUMAN PRESCRIPTION DRUG LABEL
Date: 20250710

ACTIVE INGREDIENTS: HYDROCORTISONE ACETATE 5 mg/1 g; LIDOCAINE HYDROCHLORIDE 30 mg/1 g
INACTIVE INGREDIENTS: STEARIC ACID; CETYL ALCOHOL; SORBITAN MONOSTEARATE; STEARYL ALCOHOL; CALCIUM ACETATE; PROPYLENE GLYCOL; ALUMINUM SULFATE; MINERAL OIL; WATER; SODIUM HYDROXIDE; PROPYLPARABEN; METHYLPARABEN; POLYSORBATE 60

59088-721 LIDOCAINE HCL 3%- HYDROCORTISONE ACETATE 0.5%

DESCRIPTION:

Lidocaine is chemically designated as acetamide, 2-(diethylamino)-N-(2,6-dimethylphenyl), and has the following structure:

Hydrocortisone acetate has a chemical name pregn-4-ene-3, 20-dione, 21-(acetyloxy)-11, 17-dihydroxy-(11β)-, and has the following structural formula:

INGREDIENTS: Lidocaine HCl 3% - Hydrocortisone Acetate 0.5% Cream Each gram contains Lidocaine HCl 30 mg, Hydrocortisone Acetate 5 mg.

Other Ingredients: Aluminum Sulfate, Aqua (Purified Water), Calcium Acetate, Cetyl Alcohol, Methylparaben, Mineral Oil, Polysorbate 60, Propylene Glycol, Propylparaben, Sodium Hydroxide, Sorbitan Stearate, Stearic Acid, Stearyl Alcohol.

CLINICAL PHARMACOLOGY:

MECHANISM OF ACTION:

Product releases lidocaine to stabilize the neuronal membrane by inhibiting the ionic fluxes required for initiation and conduction of impulses, thereby effecting local anesthetic action. Hydrocortisone acetate provides relief of inflammatory and pruritic manifestations of corticosteroid responsive dermatoses.

PHARMACOKINETICS:

Lidocaine may be absorbed following topical administration to mucous membranes, its rate and extent of absorption depending upon the specific site of application, duration of exposure, concentration, and total dosage. In general, the rate of absorption of local anesthetic agents following topical application occurs most rapidly after intratracheal administration. Lidocaine is also well-absorbed from the gastrointestinal tract, but little intact drug appears in the circulation because of biotransformation of the liver.
Lidocaine is metabolized rapidly by the liver, and metabolites and unchanged drug are excreted by the kidneys. Biotransformation includes oxidative N-dealkylation, ring hydroxylation, cleavage of the amide linkage, and conjungation. N-dealkylation, a major pathway of biotransformation, yields the metabolites monoethylglycinexylidide and glycinexylidide. The pharmacological/toxicological actions of these metabolites are similar to, but less potent than, those of lidocaine. Approximately 90% of lidocaine administered is excreted in the form of various metabolites, and less than 10% is excreted unchanged. The primary metabolite in urine is a conjugate of 4-hydroxy-2, 6-dimethylaniline.
The plasma binding of lidocaine is dependent of drug concentration, and the fraction bound decreases with increasing concentration. At concentrations of 1 to 4 g of free base per mL, 60 to 80 percent of lidocaine is protein bound. Binding is also dependent on the plasma concentration of the alpha-1-acid-glycoprotein.
Lidocaine crosses the blood-brain and placental barriers, presumably by passive diffusion.
Studies of lidocaine metabolism following intravenous bolus injections have shown that the elimination half-life of this agent is typically 1.5 to 2 hours. Because of the rapid rate at which lidocaine is metabolized, any condition that affects liver function may alter lidocaine kinetics. The half-life may be prolonged two-fold or more in patients with liver dysfunction. Renal dysfunction does not affect lidocaine kinetics but may increase the accumulation of metabolites.
Factors such as acidosis and the use of CNS stimulants and depressants affect the CNS levels of lidocaine required to produce overt systemic effects. Objective adverse manifestations become increasingly apparent with increasing venous plasma levels above 6 g free base per mL. In the rhesus monkey arterial blood levels of 18-21 g/mL have been shown to be the threshold for convulsive activity.
The extent of percutaneous absorption of topical corticosteroids is determined by many factors including the vehicle, the integrity of the epidermal barrier, and the use of occlusive dressings.
Topical corticosteroids can be absorbed from normal intact skin. Inflammation and/or other disease processes in the skin increase percutaneous absorption. Occlusive dressings substantially increase the percutaneous absorption of topical corticosteroids. Thus, occlusive dressings may be a valuable therapeutic adjunct for treatment of resistant dermatoses.
Once absorbed through the skin, topical corticosteroids are handled through pharmacokinetic pathways similar to systemically administered corticosteroids. Corticosteroids are bound to plasma protein in varying degrees. Corticosteroids are metabolized primarily in the liver and are then excreted by the kidneys. Some of the topical corticosteroids and their metabolites are also excreted into the bile.

INDICATIONS:

Indicated for the anti-inflammatory and anesthetic relief of itching, pain, soreness and discomfort due to hemorrhoids, anal fissures, pruritus ani and similar conditions of the anal area.

CONTRAINDICATIONS:

Product should not be used in patients with a history of sensitivity to any of its ingredients or adverse reactions to lidocaine or amide anesthetics, which usually do not cross-react with “caine” ester type anesthetics. If excessive irritation and significant worsening occur, discontinue use and seek the advice of your physician. Product and topical lidocaine should be used cautiously in those with impaired liver function, as well as the very ill or very elderly and those with significant liver disease. Product should be used with caution in patients receiving antiarrhythmic drugs of Class I since the adverse effects are additive and generally synergistic. Product is contraindicated for tuberculous or fungal lesions or skin vaccinia, varicella and acute herpes simplex. Topical corticosteroids are contraindicated in those patients with a history of hypersensitivity to any of the components of the preparation.

WARNINGS:

For external use only. Not for ophthalmic use.Product and used applicators could harm small children if chewed or swallowed.
KEEP THIS AND ALL MEDICATIONS OUT OF THE REACH OF CHILDREN.
Topical formulations of lidocaine may be absorbed to a greater extent through mucous membranes and abraded, fissured or irritated skin than through intact skin. Product should not be ingested or applied into the mouth, inside of the nose or in the eyes. Product should not be used in the ears. Any situation where lidocaine penetrates beyond the tympanic membrane into the middle ear is contraindicted because of ototoxicty associated with lidocaine observed in animals when instilled in the middle ear. Product should not come into contact with the eye or be applied into the eye because of the risk of severe eye irritation and the loss of eye surface sensation, which reduces protective reflexes and can lead to corneal irritation and possibly abrasion. If eye contact occurs, rinse out the eye immediately with saline or water and protect the eye surface until sensation is restored.

PRECAUTIONS:

If irritation or sensitivity occurs or infection appears, discontinue use and institute appropriate therapy. If extensive areas are treated, the possibility of systemic absorption exists. Systemic absorption of topical steroids has produced reversible hypothalamic-pituitary-adrenal (HPA) axis suppression, manifestation of Cushing’s syndrome, hyperglycemia, and glycosuria in some patients. Conditions which augment systemic absorption include the application of the more potent steroids, use over large surface areas, prolonged use, and the addition of occlusive dressings. Therefore, patients receiving a large dose of potent topical steroids applied to a large surface area, or under an occlusive dressing, should be evaluated periodically for evidence of HPA axis suppression. If noted, an attempt should be made to withdraw the drug, to reduce the frequency of application, or to substitute a less potent steroid. Recovery of the HPA axis function is generally prompt and complete upon discontinuation of the drug. Infrequently, signs and symptoms of steroid withdrawal may occur, requiring supplemental systemic corticosteroids. Children may absorb proportionately larger amounts of topical corticosteroids and thus be more susceptible to systemic toxicity. If irritation develops, topical steroids should be discontinued and appropriate therapy instituted. In the presence of dermatological infections, the use of an appropriate antifungal or antibacterial agent should be instituted. If a favorable response does not occur promptly, the corticosteroid should be discontinued until the infection has been adequately controlled.

CARCINOGENESIS, MUTAGENESIS, AND IMPAIRMENT OF FERTILITY:

Long-term animal studies have not been performed to evaluate the carcinogenic potential or the effect on fertility of topical corticosteroids. Studies to determine mutagenicity with prednisolone and hydrocortisone have revealed negative results. Studies of lidocaine in animals to evaluate the carcinogenic and mutagenic potential of the effect on fertility have not been conducted.

USE IN PREGNANCY:

Teratogenic Effects:

Pregnancy Category C Reproduction studies have been performed for lidocaine in rats at doses up to 6.6 times the human dose and have revealed no evidence of harm to the fetus caused by lidocaine. There are, however, no adequate and well-controlled studies in pregnant women. Animal reproduction studies are not always predictive of human response. General consideration should be given to this fact before administering lidocaine to women of childbearing potential, especially during early pregnancy when maximum organogenesis takes place. Corticosteroids are generally teratogenic in laboratory animals when administered systemically at relatively low dosage levels. The more potent corticosteroids have been shown to be teratogenic after dermal application in laboratory animals. There are no adequate and well controlled studies in pregnant women on teratogenic effects from topically applied corticosteroids. Therefore, topical corticosteroids should be used during pregnancy only if the potential benefit justifies the potential risk to the fetus. Drugs of this class should not be used extensively on pregnant patients, in large amounts or for prolonged periods of time.

NURSING MOTHERS:

It is not known whether this drug is excreted in human milk. Because many drugs are excreted in human milk, caution should be exercised when this drug is administered to a nursing mother.

PEDIATRIC USE:

Safety and efficacy in children have not been established.

ADVERSE REACTIONS:

During or immediately following application of product, there may be transient stinging or burning from open areas of skin, or transient blanching (lightening), or erythema (redness) of the skin.

DOSAGE AND ADMINISTRATION:

Apply product to the affected area(s) twice daily or as directed by a licensed healthcare practitioner.

Product should not be used in excess of recommendations or for prolonged use in the anal canal. If the condition does not respond to repeated courses of product or should worsen, discontinue use and seek the advice of your licensed healthcare practitioner.

Use under the direction of a licensed healthcare practitioner.

Products without Applicators: Remove the child-resistant cap and foil seal from the tube. Apply a thin film to the affected area. Replace the cap after use.

Products with Single-Use Tubes and Applicators: Tear open one cleansing wipe packet (if the product kit contains such item), gently clean the affected area and discard the used cleansing wipe. Remove the child-resistant cap and foil seal from one tube and firmly screw one applicator onto the tube. Do not overtighten. Squeeze the tube to fill the applicator until a small amount of cream comes out of and lubricates the applicator openings. Gently insert the applicator tip with attached tube into anal area. Continue squeezing the body of the tube as it is moved around the areas of discomfort, and lastly, around and in the anal opening (if directed by physician). Do not completely insert the applicator and tube into the anus or insert deep into the rectum. Do not insert a loose applicator tip into the anus or rectum. Once application is completed, both the tube and applicator should be gently removed and discarded.

HOW SUPPLIED:

Lidocaine HCl 3% + Hydrocortisone Acetate 0.5% Cream

Kit contains 20 Single-Use ¼ oz (7g) Tubes (NDC 59088-819-01), Applicators (20ct) and Cleansing Wipes (20ct). NDC 59088-721-00.

KEEP THIS AND ALL MEDICATIONS OUT OF REACH OF CHILDREN.

Store at 20º-25ºC (68º-77ºF) [see USP Controlled Room Temperature]. Protect from freezing.

Lidocaine HCl 3% + Hydrocortisone Acetate 0.5% Cream

Manufactured by:
PureTek Corporation
Panorama City, CA 91402
For questions or information
call toll-free: 877-921-7873